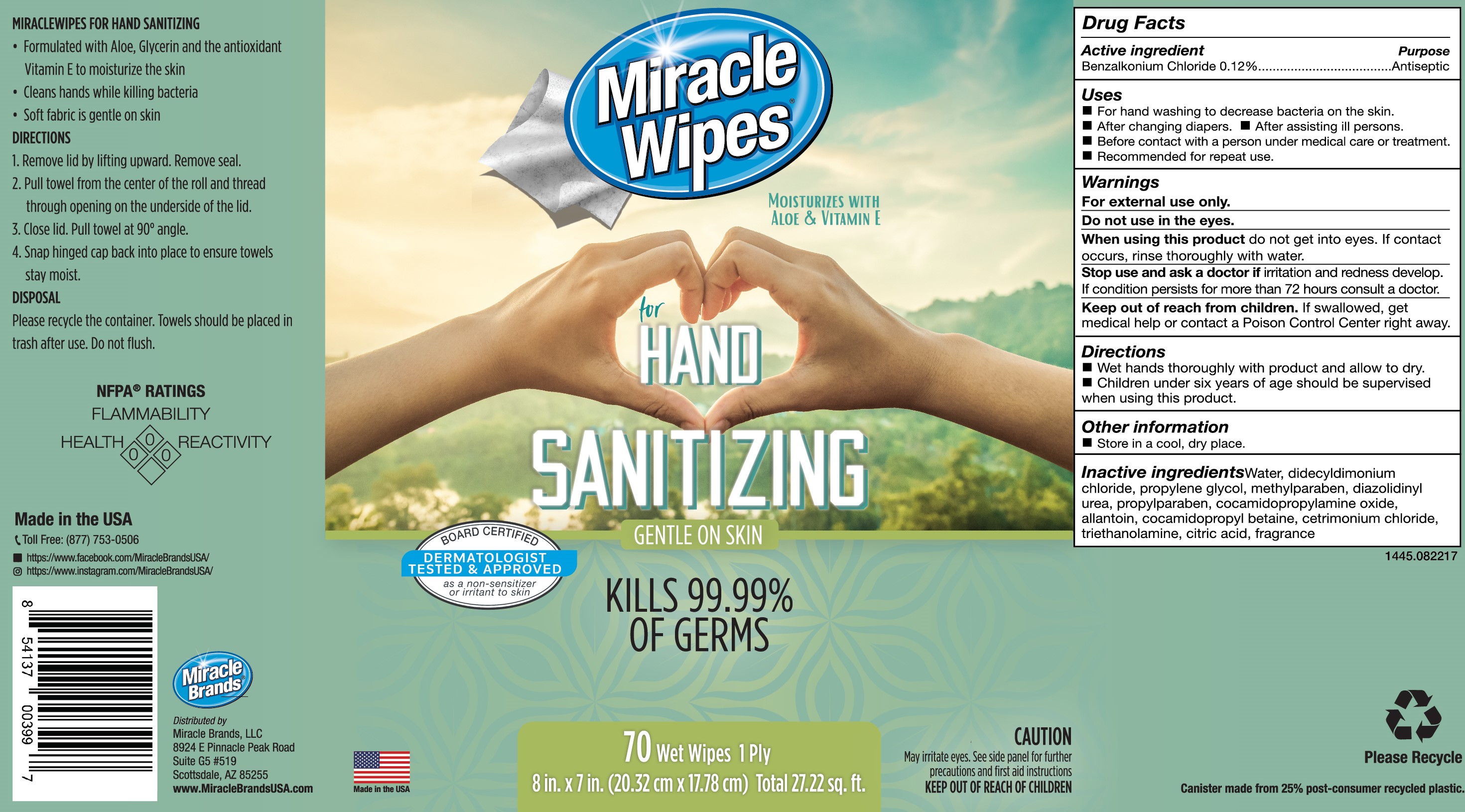 DRUG LABEL: Miracle Wipes for Hand Sanitizing
NDC: 79779-002 | Form: CLOTH
Manufacturer: Kelly Products, Inc.
Category: otc | Type: HUMAN OTC DRUG LABEL
Date: 20210211

ACTIVE INGREDIENTS: BENZALKONIUM CHLORIDE 0.13 g/100 g
INACTIVE INGREDIENTS: DIDECYLDIMONIUM CHLORIDE; TROLAMINE; ALOE; CITRAL; WATER; COCAMIDOPROPYLAMINE OXIDE; CETRIMONIUM CHLORIDE; PROPYLENE GLYCOL; DIAZOLIDINYL UREA; METHYLPARABEN; ANHYDROUS CITRIC ACID; ORANGE TERPENES; ALPHA-TOCOPHEROL; ALLANTOIN; COCAMIDOPROPYL BETAINE

Miracle Wipe for Hand Sanitizing

Active Ingredient(s)

Benzalkonium Chloride 0.13%

Purpose

Antiseptic, Hand Sanitizer

Use

Hand Sanitizer to help reduce bacteria that potentially can cause disease.

Warnings

For external use only. Flammable. Keep away from heat or flame

Do not use

- in the eyes

When using this product do not get into eyes. In case of contact with eyes, rinse eyes thoroughly with water.

Stop use and ask a doctor if irritation and redness develop. If condition persists for more than 72 hours consult a doctor.

Keep out of reach of children. If swallowed, get medical help or contact a Poison Control Center right away.

Directions

- Wet hands thoroughly with product and allow to dry.
- Children under six years of age should be surprised when using this product.

Other information

- Store in a cool, dry place.

Inactive ingredients

Water, Cocamidopropyl Betaine, Cetrimonium Chloride, Didecyldimonium Chloride, Allantoin, Fragrance, Aloe, Cocamidopropylamine Oxide, Propylene Glycol, Diazolidinyl Urea, Methylparaben, Propylparaben, Triethonalamine, Vitamin E, Citric Acid

Package Label - Principal Display Panel

70 Wet Wipes 1 Ply NDC: 79779-002-70